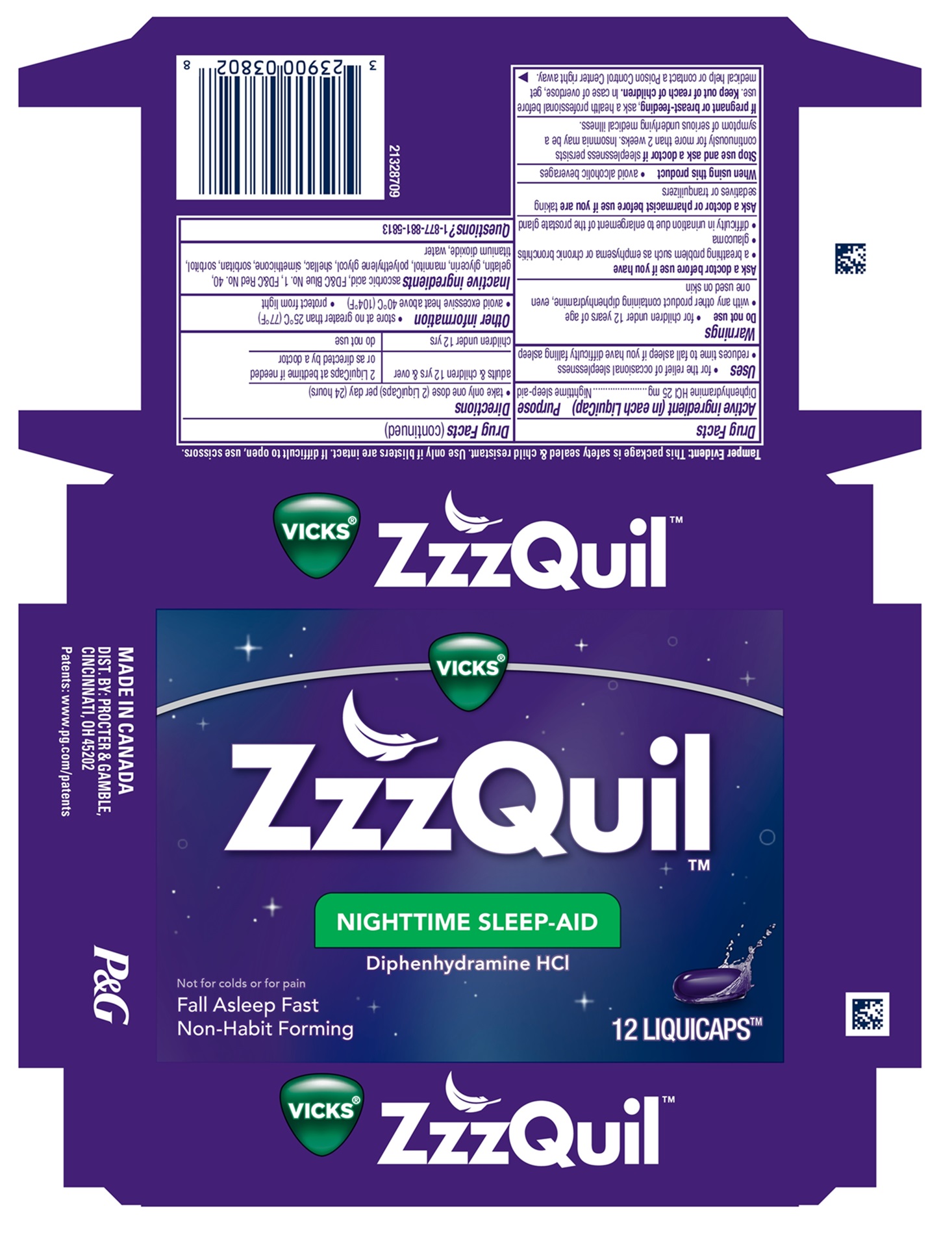 DRUG LABEL: ZzzQuil
NDC: 37000-501 | Form: CAPSULE, GELATIN COATED
Manufacturer: The Procter & Gamble Manufacturing Company
Category: otc | Type: HUMAN OTC DRUG LABEL
Date: 20251001

ACTIVE INGREDIENTS: DIPHENHYDRAMINE HYDROCHLORIDE 25 mg/1 1
INACTIVE INGREDIENTS: DIMETHICONE; FD&C BLUE NO. 1; GELATIN; GLYCERIN; POLYETHYLENE GLYCOL, UNSPECIFIED; WATER; FD&C RED NO. 40; TITANIUM DIOXIDE; MANNITOL; SHELLAC; SORBITAN; ASCORBIC ACID

ZzzQuil™NIGHTTIME SLEEP-AID LIQUICAPS

Drug Facts

Active ingredients (in each liquicap)

Diphenhydramine HCl 25 mg

Purpose

Nighttime sleep-aid

Uses

- for the relief of occasional sleeplessness
- reduces time to fall asleep if you have difficulty falling asleep

Warnings

Do not use

- for children under 12 years of age
- with any other product containing diphenhydramine, even one used on skin.

Ask a doctor before use if you have

- a breathing problem such as emphysema or chronic bronchitis
- glaucoma
- difficulty in urination due to enlargement of the prostate gland

Ask a doctor or pharmacist before use if you are taking sedatives or tranquilizers

When using this product

- avoid alcoholic beverages

Stop use and ask a doctor if sleeplessness persists continuously for more than 2 weeks. Insomnia may be a symptom of serious underlying medical illness.

PREGNANCY OR BREAST FEEDING

If pregnant or breast-feeding, ask a health professional before use.

Keep out of reach of children.

OVERDOSAGE

In case of overdose, get medical help or contact a Poison Control Center right away.

Directions

• take only one dose (2 LiquiCaps) per day (24 hours)

adults & children 12 yrs & over | 2 LiquiCaps at bedtime if needed or as directed by a doctor
children under 12 yrs | do not use

Other information

- store at no greater than 25°C (77°F)
- avoid excessive heat above 40°C (104°F)
- protect from light

Inactive ingredients

asorbic acid, FD&C Blue No. 1, FD&C Red No. 40, gelatin, glycerin, mannitol, polyethylene glycol, shellac, simethicone, sorbitan, sorbitol, titanium dioxide, water

Questions?

1-877-881-5813

Tamper Evident: This package is safety sealed & child resistant. Use only if blisters are intact. If difficult to open, use scissors.

MADE IN CANADA.

DIST. BY: PROCTER & GAMBLE,

CINCINNATI, OH 45202

PRINCIPAL DISPLAY PANEL - 12 LiquiCap Carton

VICKS®

ZzzQuil™
NIGHTTIME SLEEP-AID
Diphenhydramine HCl

Not for colds or for pain

Fall Asleep Fast

Non-Habit Forming

12 LIQUICAPS™